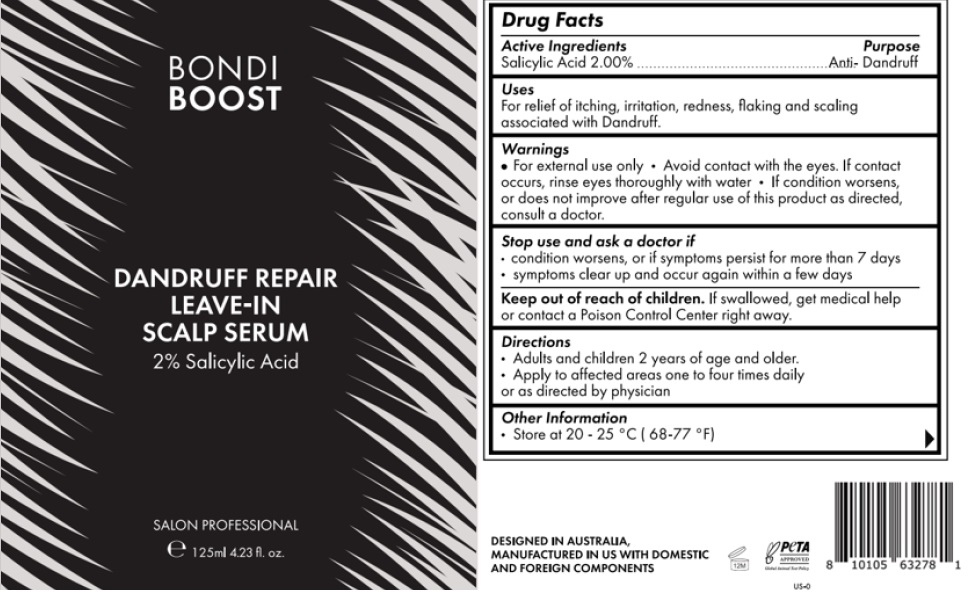 DRUG LABEL: Bondiboost scalp serum
NDC: 84169-004 | Form: LIQUID
Manufacturer: Bondi Boost US LLC
Category: otc | Type: HUMAN OTC DRUG LABEL
Date: 20241223

ACTIVE INGREDIENTS: SALICYLIC ACID 20 mg/1 mL
INACTIVE INGREDIENTS: GLYCERIN; PENTYLENE GLYCOL; PEPPERMINT OIL; MATRICARIA CHAMOMILLA WHOLE; XANTHAN GUM; HYDROLYZED JOJOBA ESTERS (ACID FORM); CAFFEINE; WATER; SODIUM HYDROXIDE; PROPANEDIOL; ALOE VERA LEAF; MENTHOL; CUCUMIS SATIVUS WHOLE; PYRITHIONE ZINC; PANTHENOL; ARNICA MONTANA FLOWER; NIACINAMIDE; CAPRYLYL GLYCOL; ETHYLHEXYLGLYCERIN

Bondi Boost Scalp Serum

Active Ingredients | Purpose
Salicylic Acid 2.00% | Anti- Dandruff

Stop use and ask a doctor if:

- Conditin worsens, or if symptoms persist for more than 7 days
- symptoms clear up and occur again within a few days

Keep out of reach of children. If swallowed, get medical help or contact a Poison Control Center right away.

Uses

For relief of itching, irritation, redness, flaking and scaling assoicated with Dandruff.

Questions? 1(877)-241-0459

Stop use and ask as doctor if

- condition worsens, or if symptoms persist for more than 7 days
- symptoms clear up and occur again within a few days

Warnings

- For external use only
- Avoid contact with the eyes. If contact occurs, rinse eyes throroughly with water.
- If condition worsens, or does not improve adter regular use of this product as directed, consult a doctor

INACTIVE INGREDIENT

Water (Aqua, Eau), Glycerin, Propanediol, Pentylene Glycol, Caprylyl Glycol, Ethylhexylglycerin, Menthol, Aloe Barbadensis Leaf Juice, Niacinamide, Zinc Pyrithione, Caffeine, Mentha Piperita (Peppermint) Oil, Arnica Montana Flower Extract, Cucumis Sativus (cucumber) Fruit Extract, Chamomilla Recutita (Matricaria) Extract, Panthenol, Xanthan Gum, Hydrolyzed Jojoba Esters, Sorbitan Oleate Decylglucoside Crosspolymer, Sodium Hydroxide.

Uses

For Relef of itching, irritaion, redness, flaking and scaling associated with Dandruff.